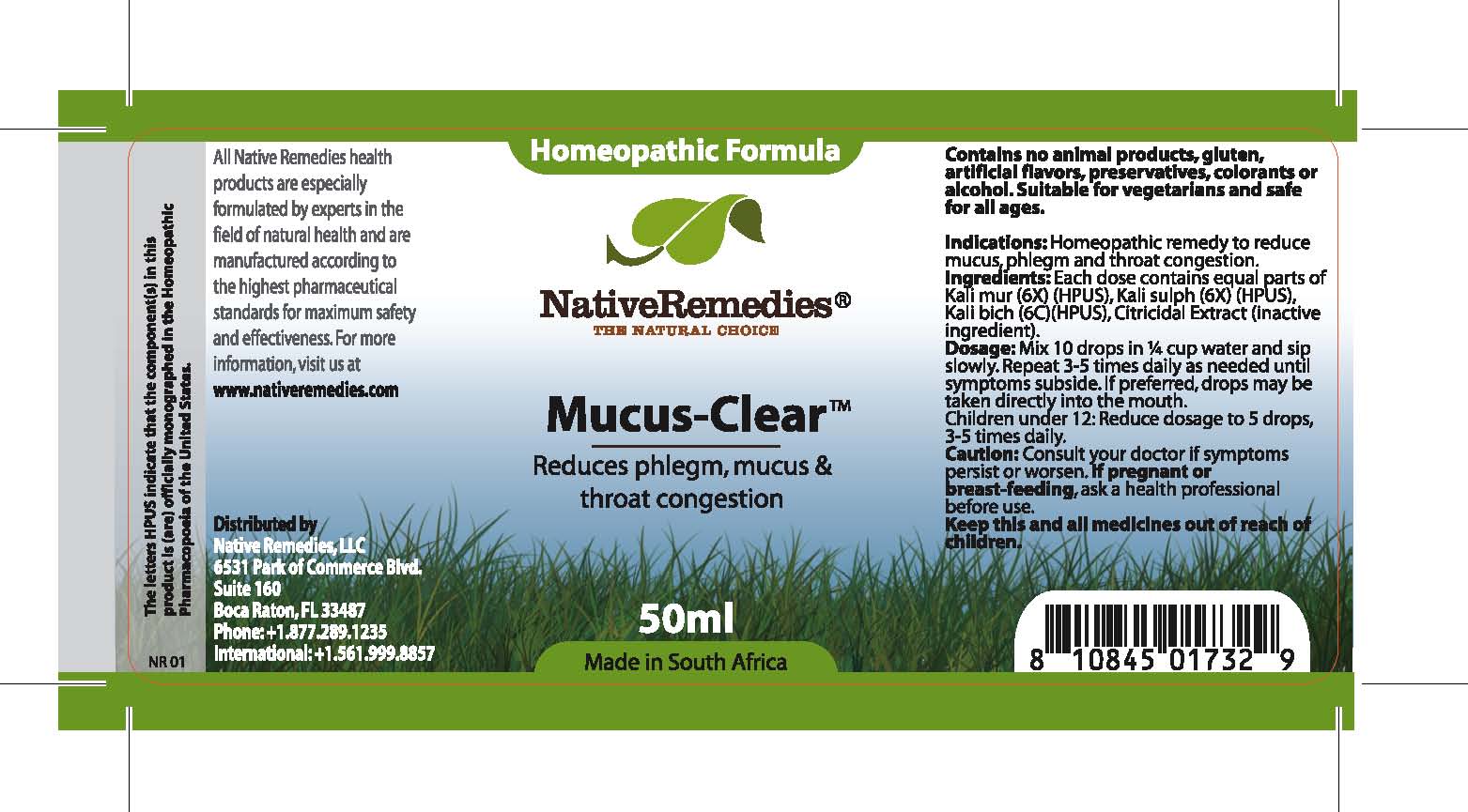 DRUG LABEL: Mucus Clear
NDC: 68647-180 | Form: TINCTURE
Manufacturer: Feelgood Health
Category: homeopathic | Type: HUMAN OTC DRUG LABEL
Date: 20100728

ACTIVE INGREDIENTS: POTASSIUM CHLORIDE 6 [hp_X]/50 mL; POTASSIUM SULFATE 6 [hp_X]/50 mL; POTASSIUM DICHROMATE 6 [hp_C]/50 mL
INACTIVE INGREDIENTS: CITRUS PARADISI SEED 0.125 mL/50 mL; WATER 49.488 mL/50 mL

MUCUS CLEAR

PURPOSE

Reduces phlegm, mucus and throat congestion

INDICATIONS AND USAGE

Indications: Homeopathic remedy to reduce mucus, phlegm and throat congestion.

DOSAGE AND ADMINISTRATION

Dosage: Mix 10 drops in ¼ cup water and sip slowly. Repeat 3-5 times daily as needed until symptoms subside. If preferred, drops may be taken directly into the mouth. Children under 12: Reduce dosage to 5 drops, 3-5 times daily.

GENERAL PRECAUTIONS

Caution: Consult your doctor if symptoms persist or worsen. Keep this and all medicines out of reach of children.

ACTIVE INGREDIENT

Ingredients: Each dose contains equal parts of Kali mur (6X) (HPUS), Kali sulph (6X) (HPUS), Kali bich (6C)(HPUS)

Citricidal Extract (inactive ingredient).

WARNINGS

Contains no animal products, gluten, artificial flavors, preservatives, colorants or alcohol. Suitable for vegetarians and safe for all ages.

PATIENT COUNSELING INFORMATION

All Native Remedies health products are especially formulated by experts in the field of natural health and are manufactured according to the highest pharmaceutical standards for maximum safety and effectiveness. For more information, visit us at www.nativeremedies.com

Distributed by

Native Remedies, LLC

6531 Park of Commerce Blvd.Suite 160

Boca Raton, FL 33487

Phone: +1.877.289.1235

International: +1.561.999.8857
The letters HPUS indicate that the component(s) in this product is (are) officially monographed in the Homeopathic Pharmacopoeia of the United States.

PREGNANCY

If pregnant or breastfeeding, ask a health professional before use.

KEEP OUT OF REACH OF CHILDREN

Keep this and all medicines out of reach of children.